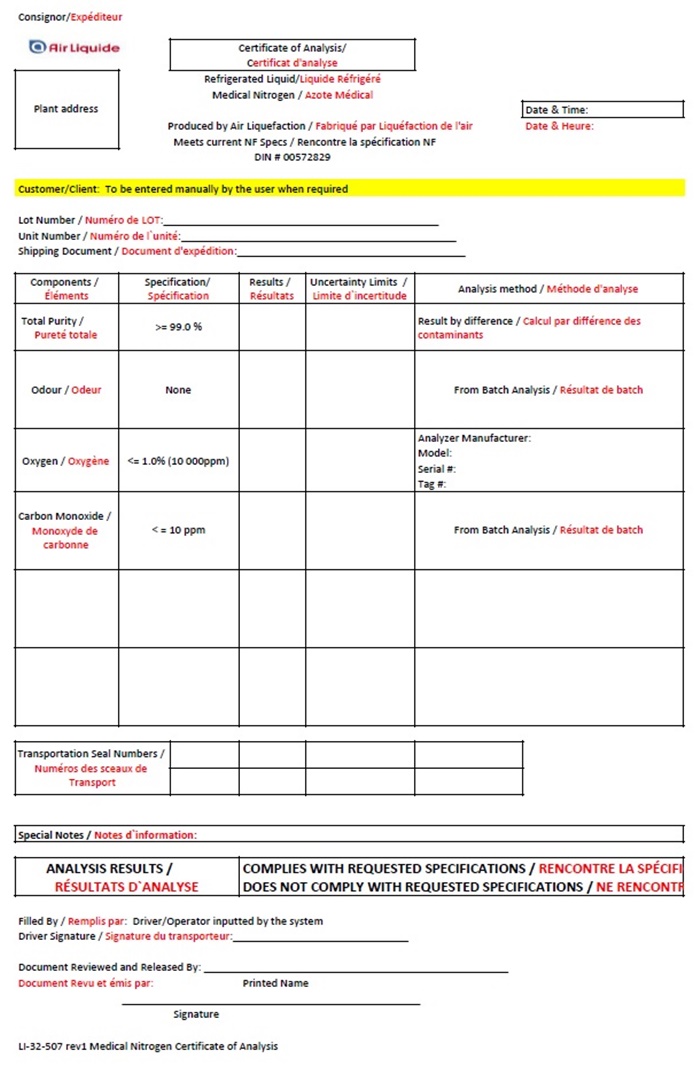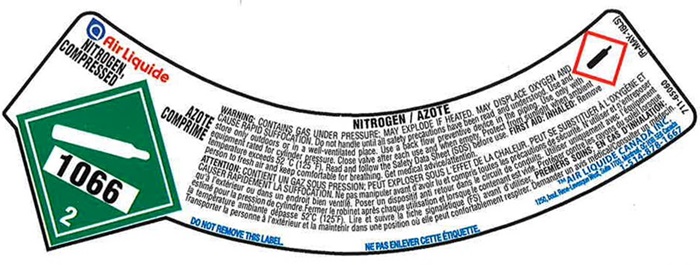 DRUG LABEL: NITROGEN
NDC: 74709-002 | Form: GAS
Manufacturer: Air Liquide Canada Inc
Category: prescription | Type: HUMAN PRESCRIPTION DRUG LABEL
Date: 20241004

ACTIVE INGREDIENTS: NITROGEN 992 mL/1 L

Air Liquide Canada Nitrogen 002

Air Liquide Canada Nitrogen

Air Liquide

NITROGEN, AZOTE

COMPRESSED COMPRIME

1066

2

NITROGEN / AZOTE

WARNING: CONTYAINS GAS UNDER PRESSURE; MAY EXPLODE IF HEATED. MAY DISPLACE OXYGEN AND CAUSE RAPID SUFFOCATION. Do not handle until all safety precautions have been read and understood. Use and store only outdoors or in a well-ventilated place. Use a back flow preventive device in the piping. Use only with equipment rated for cylinder pressure. Close valve after each use and when empty. Protect from sunlight when ambient temperature exceeds 52°C (125°F). Read and follow the Safety Data Sheet (SDS) before use. FIRST AID; INHALED: Remove person to fresh air and keep comfortable for breathing. Get medical advice/attention.

ATTENTION: CONTIENT UNGAZ SOUS PRESSION; PEUT EXPLOSER SOUS L’EFFET DE LACHALEUR, PEUT SE SUBSTITUER A L’OXGENE ET CAUSER RAPIDEMENT LA SUFFOCATION. Ne pas manipuler avant d’avoir lu et compris toutes les precautins de securite. N’utiliser et e’entreposer qu’a l’exterieur ou dans un endroit bien ventile. Poser un dispositive anti retour dans le circuit de conduits. Utilser uniquement avec l’equipment estime pour la pression de cylinder. Fermer le robinet apres chaque utilization et lorsque le contenant est vide. Proteger contre les rayons du solell lorsque la temperature ambiante depasse 52°C (125°F). Lire et suivre la tiche signatetique (FS) avant d’utiliser. PREMIERS SOINS; EN CAS D’INHALATION; Transporter la personnne a l’exterieur et la maintenir dans une position ou elle peut confortablement respire. Demander un avis medical /Consultr un medecin.

DO NOT REMOVE THIS LABEL NE PAS ENLEVER CETTE ÉTIQUETTE.

™AIR LIQUIDE CANADA INC.

1250 René-Levesque West, Suite 1700, Montreal, OC H3B 5E6 Canada

1-514-878-1667

Air Liquide Canada Nitrogen COA

Consignor/ Expèditeur

Air Liquide Certificate of Analysis

Certificat d’analyse

Plant Address Refrigerated Liquid / Liquide Réfrigéré

Medical Nitrogen / Azote Médical

Date & Time

Date & Heure:

Produced by Air Liquefaction / Fabriqué par Liquéfaction de l’air

Meets current NF Specs / Rencontre la spécifcation NF

DIN # 00572829

Customer/Client: To be entered manually by the user when required

Lot Number / Numéro de LOT: __________________

Unit Number / Numéro de l’unité: _______________

Shipping Document / Document d’expédition: ________________

Componets /; Éléments | Specification /; Specification | Results /; Résultats | Uncertainty Limits /; Limite d’incertitude | Analysis method / Méthode d’analyse
Total Purity / Pureté totale | >=99.0% |  |  | Result by difference / Calcul par difference des contaminants
Odour / Odeur | None |  |  | From Batch Analysis / Résultat de batch
Oxygen / Oxygéne | <=1.0% (10000ppm) |  |  | Analyzer Manufacturer:; Model:; Serial #:; Tag #:
Carbon Monoxide / Monoxyde de carbonne | <=10 ppm |  |  | From Batch Analysis / Résultat de batch

Transportation Seal Numbers / Numéros des sceaux de Transport

Special Notes / Notes d’information:

ANALYSIS RESULTS /

RÉSULTATS D’ANALYSE

COMPLIES WITH REQUESTED SPECIFICATIONS / RENCONTRE LA SPÉCIFICATION

DOES NOT COMPLY WITH REQUESTED SPECIFICATIONS / NE RECONTR

Filled By / Remplis par: Driver / Operator inputted by the system

Driver Signature / Signature du transporteur: ______________________________

Document Reviewed and Released By: ___________________________________

Printed Name

Document Revu et émis par:

______________________________________________________

Signature

LI-32-507 rev 1 Medical Nitrogen Certificate of Analysis